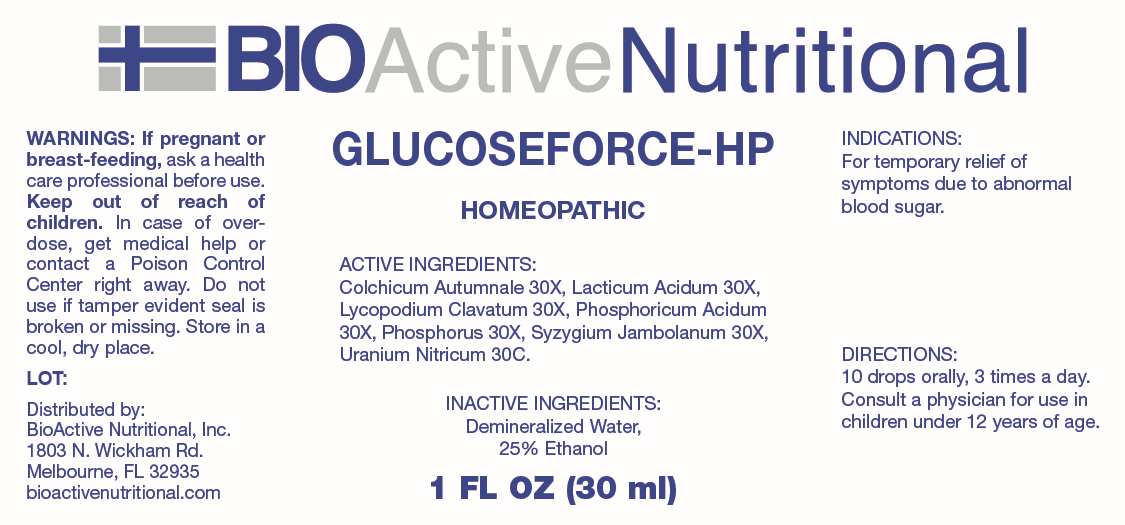 DRUG LABEL: Glucoseforce
NDC: 43857-0648 | Form: LIQUID
Manufacturer: BioActive Nutritional, Inc.
Category: homeopathic | Type: HUMAN OTC DRUG LABEL
Date: 20241118

ACTIVE INGREDIENTS: COLCHICUM AUTUMNALE BULB 30 [hp_X]/1 mL; LACTIC ACID, DL- 30 [hp_X]/1 mL; LYCOPODIUM CLAVATUM SPORE 30 [hp_X]/1 mL; PHOSPHORIC ACID 30 [hp_X]/1 mL; PHOSPHORUS 30 [hp_X]/1 mL; SYZYGIUM CUMINI SEED 30 [hp_X]/1 mL; URANYL NITRATE HEXAHYDRATE 30 [hp_C]/1 mL
INACTIVE INGREDIENTS: WATER; ALCOHOL

DRUG FACTS:

ACTIVE INGREDIENTS:

Colchicum Autumnale 30X, Lacticum Acidum 30X, Lycopodium Clavatum 30X, Phosphoricum Acidum 30X, Phosphorus 30X, Syzygium Jambolanum 30X, Uranium Nitricum 30C.

PURPOSE:

For temporary relief of symptoms due to abnormal blood sugar.

WARNINGS:

If pregnant or breast-feeding, ask a health care professional before use.

Keep out of reach of children. In case of overdose, get medical help or contact a Poison Control Center right away.

Do not use if tamper evident seal is broken or missing.

Store in a cool, dry place.

KEEP OUT OF REACH OF CHILDREN:

In case of overdose, get medical help or contact a Poison Control Center right away.

DIRECTIONS:

10 drops orally, 3 times a day. Consult a physician for use in children under 12 years of age.

INDICATIONS:

For temporary relief of symptoms due to abnormal blood sugar.

INACTIVE INGREDIENTS:

Demineralized Water, 25% Ethanol

QUESTIONS:

Distributed by:
BioActive Nutritional, Inc.
1803 N. Wickham Rd.
Melbourne, FL 32935
bioactivenutritional.com

PACKAGE LABEL DISPLAY:

BIOActiveNutritional

GLUCOSEFORCE-HP

HOMEOPATHIC

1 FL OZ (30 ml)